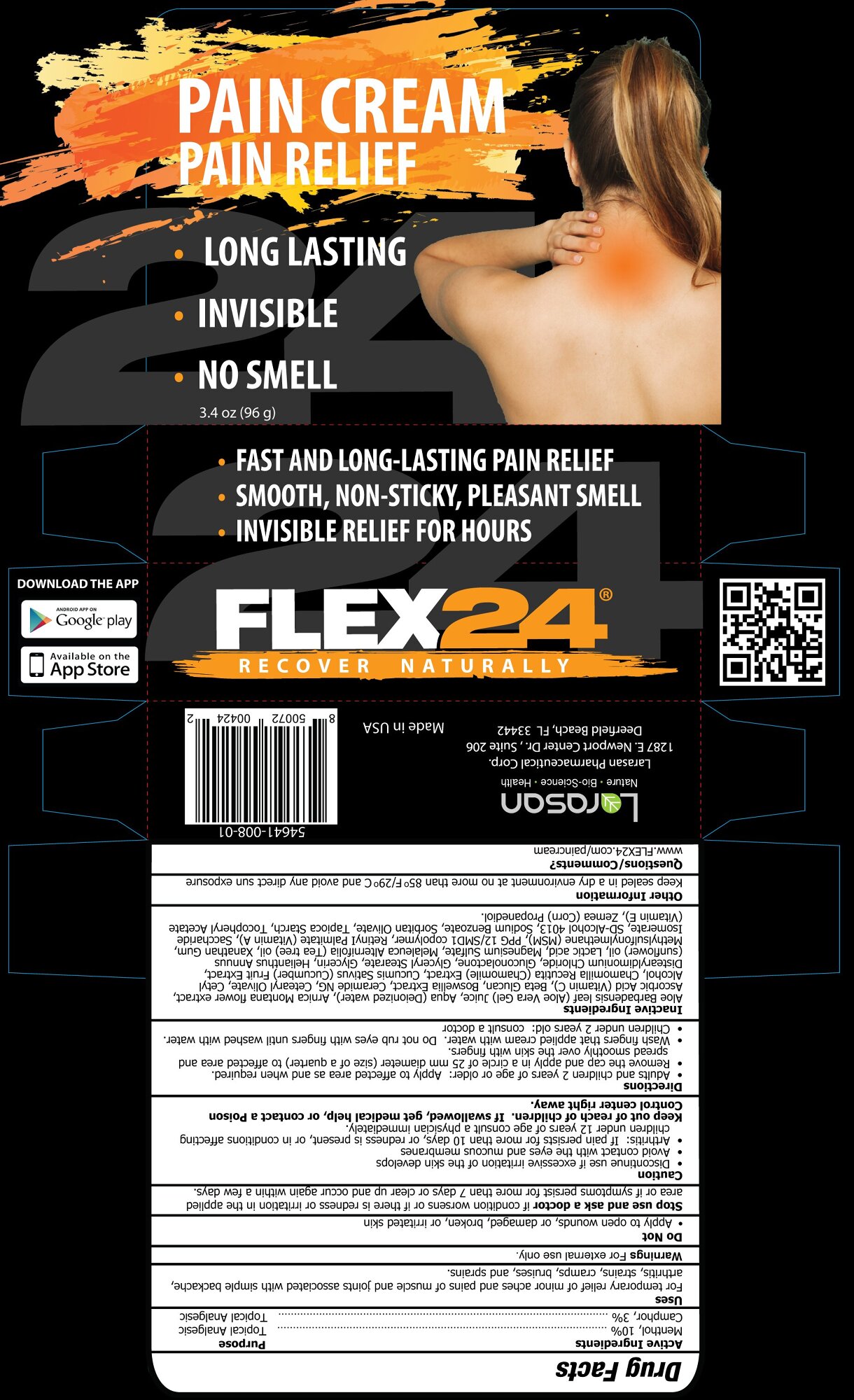 DRUG LABEL: Flex24 Pain
NDC: 54641-008 | Form: CREAM
Manufacturer: Larasan Pharmaceutical Corporation
Category: otc | Type: HUMAN OTC DRUG LABEL
Date: 20190222

ACTIVE INGREDIENTS: CAMPHOR (NATURAL) 3 1/100 g; MENTHOL 10 g/100 g
INACTIVE INGREDIENTS: ALOE VERA LEAF; WATER; ARNICA MONTANA; ASCORBIC ACID; GLUCAN ENDO-1,3-.ALPHA.-GLUCOSIDASE AGN1; BOSWELLIA SERRATA WHOLE; CERAMIDE NG; CETEARYL OLIVATE; CETYL ALCOHOL; MATRICARIA CHAMOMILLA LEAF; CUCUMIS SATIVUS WHOLE; DISTEARYLDIMONIUM CHLORIDE; GLUCONOLACTONE; GLYCERYL STEARATE SE; GLYCERIN; SUNFLOWER OIL; LACTIC ACID, L-; MAGNESIUM SULFATE ANHYDROUS; TEA TREE OIL; XANTHAN GUM; DIMETHYL SULFONE; PPG-12/SMDI COPOLYMER; VITAMIN A; SACCHARIDE ISOMERATE; ALCOHOL; DENATONIUM BENZOATE; TERT-BUTYL ALCOHOL; SODIUM BENZOATE; SORBITAN OLIVATE; STARCH, TAPIOCA; .ALPHA.-TOCOPHEROL ACETATE; PROPANEDIOL

Active Ingredients

Menthol, 10%
Camphor, 3%

Purpose

Topical analgesic

Uses

For temporary relief of minor aches and pains of muscle and joints associated with simple backache, arthritis, strains, cramps, bruises, and sprains.

Warnings

For external use only

Do not

• Apply to open wounds, or damaged, broken, or irritated skin

Stop use and ask a doctor if condition worsens or if there is redness or irritation in the applied area or if symptoms persist for more than 7 days or clear up and occur again within a few days.

Caution

• Discontinue use if excessive irritation of the skin develops
• Avoid contact with the eyes and mucous membranes
• Arthritis: If pain persists for more than 10 days, or redness is present, or in conditions affecting children under 12 years of age consult a physician immediately.

Keep out of reach of children. If swallowed, get medical help or contact a Poison Control Center right away.

Directions

• Adults and children 2 years of age or older: Apply to affected area as and when required.
• Remove the cap and apply in a circle of 25 mm diameter (size of a quarter) to affected area and spread smoothly over the skin with fingers.
• Wash fingers that applied cream with water. Do not rub eyes with fingers until washed with water.
• Children under 2 years old: consult a doctor

Inactive Ingredients

Aloe Barbadensis leaf (Aloe Vera Gel) Juice, Aqua (Deionized water), Arnica Montana flower extract, Ascorbic Acid (Vitamin C), Beta Glucan, Boswellia Extract, Ceramide NG, Cetearyl Olivate, Cetyl Alcohol, Chamomilla Recutita (Chamomile) Extract, Cucumis Sativus (Cucumber) Fruit Extract, Distearyldimonium Chloride, Gluconolactone, Glyceryl Stearate, Glycerin, Helianthus Annuus (sunflower) oil, Lactic acid, Magnesium Sulfate, Melaleuca Alternifolia (Tea tree) oil, Xanathan Gum, Methylsulfonylmethane (MSM), PPG 12/SMD1 copolymer, Retinyl Palmitate (Vitamin A), Saccharide Isomerate, SD-Alcohol 4013, Sodium Benzoate, Sorbitan Olivate, Tapioca Starch, Tocopheryl Acetate (Vitamin E), Zemea (Corn) Propanediol

Other Information

Keep sealed in a dry environment at no more than 85°F/29°C and avoid any direct sun exposure

Questions/Comments?

www.FLEX24.com/paincream

Larasan Pharmaceutical Corp.

1287 E. Newport Center Drive, Suite 206

Deerfield Beach, FL 33442

Made in USA

54641-008-01

PACKAGE LABEL

Pain Cream

Pain Relief

- Long Lasting
- Invisible
- No smell

3.4 oz (96 g)

- Fast and Long-Lasting Pain Relief
- Smooth, Non-Sticky, Pleasant Smell
- Invsible Relief for Hours

Flex24(r)

Recover Naturally